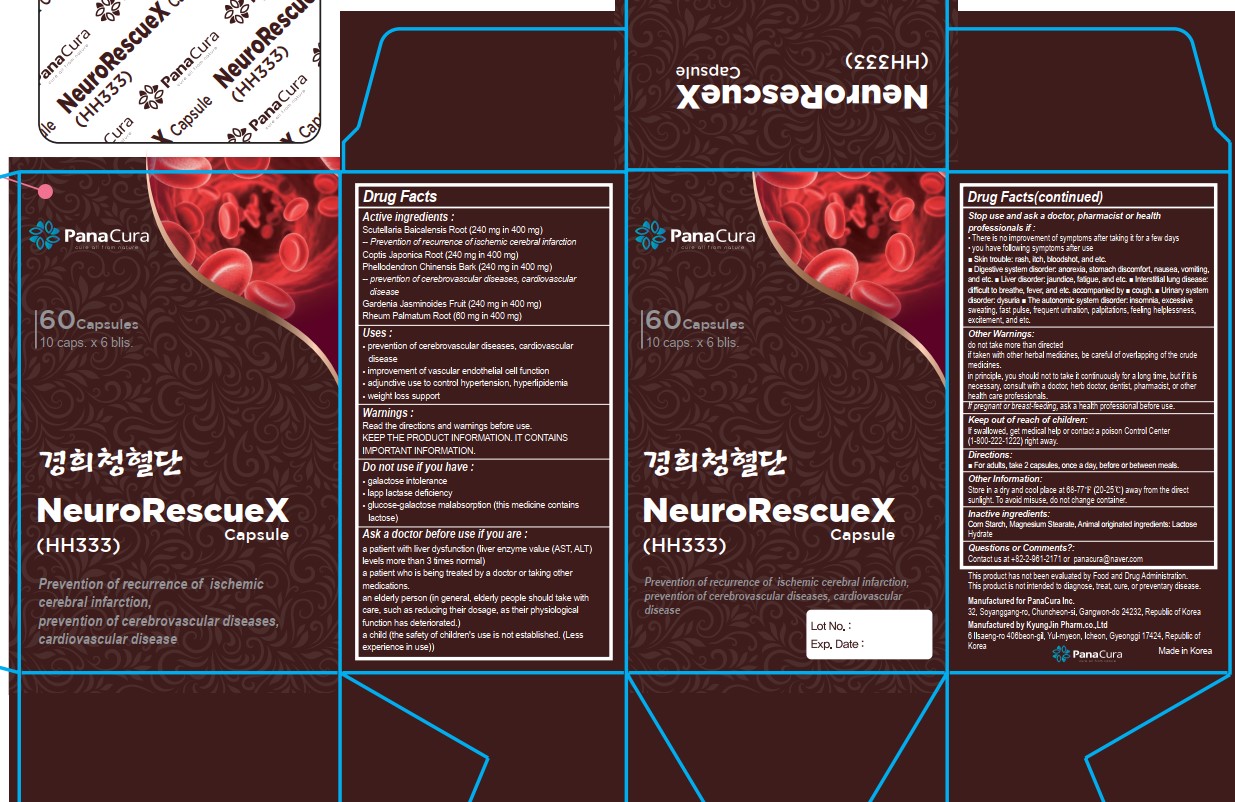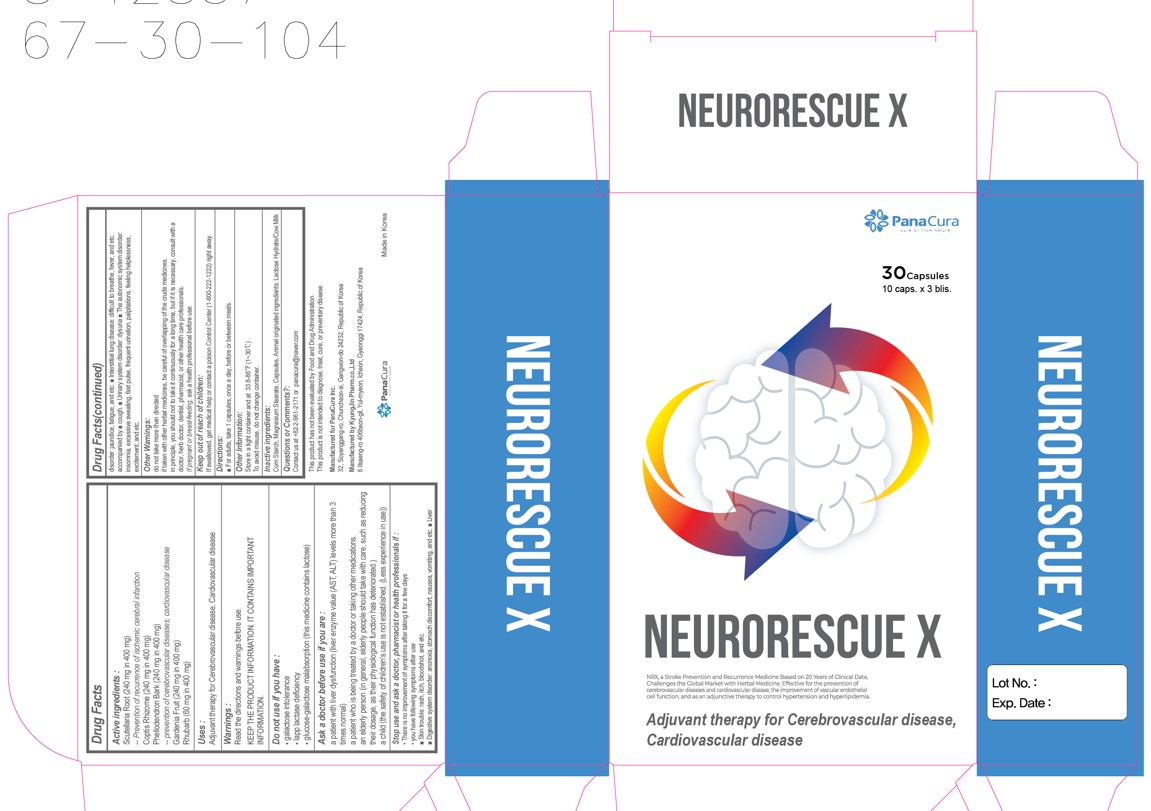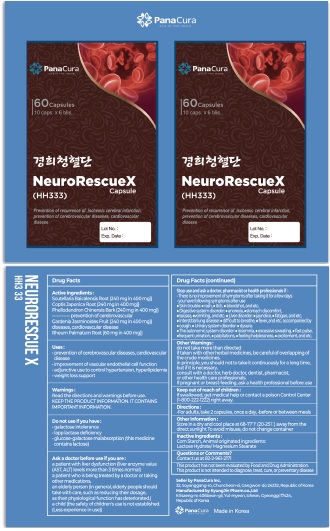 DRUG LABEL: NeuroRescueX HH333
NDC: 84074-001 | Form: CAPSULE
Manufacturer: Panacura Inc.
Category: otc | Type: HUMAN OTC DRUG LABEL
Date: 20251209

ACTIVE INGREDIENTS: SCUTELLARIA BAICALENSIS ROOT 240 mg/1 1; COPTIS JAPONICA ROOT 240 mg/1 1; PHELLODENDRON CHINENSIS BARK 240 mg/1 1; GARDENIA JASMINOIDES FRUIT 240 mg/1 1; RHEUM PALMATUM ROOT 60 mg/1 1
INACTIVE INGREDIENTS: STARCH, CORN; MAGNESIUM STEARATE; LACTOSE MONOHYDRATE

84074-001_NeuroRescueX HH333

DOSAGE AND ADMINISTRATION

■ For adults, take 2 capsules, once a day, ■ before or between meals

ACTIVE INGREDIENT

Scutellaria Baicalensis Root (240 mg in 400 mg)
Coptis Japonica Root (240 mg in 400 mg)
Phellodendron Chinensis Bark (240 mg in 400 mg)
Gardenia Jasminoides Fruit (240 mg in 400 mg)
Rheum Palmatum Root (60 mg in 400 mg)

PURPOSE

prevention of cerebrovascular diseases, cardiovascular disease

Do not use if you have
■ galactose intolerance
■ lapp lactase deficiency
■ glucose-galactose malabsorption (this medicine contains lactose)

Ask a doctor before use if you are
a patient with liver dysfunction (liver enzyme value (AST, ALT) levels more than 3 times normal)
a patient who is being treated by a doctor or taking other medications.
an elderly person (in general, elderly people should take with care, such as reducing their dosage, as their physiological function has deteriorated.)
a child (the safety of children's use is not established. (Less experience in use))

INDICATIONS AND USAGE

■ prevention of cerebrovascular diseases, cardiovascular disease
■ improvement of vascular endothelial cell function
■ adjunctive use to control hypertension, hyperlipidemia
■ weight loss support

Read the directions and warnings before use.
KEEP THE PRODUCT INFORMATION. IT CONTAINS IMPORTANT INFORMATION.

Stop use and ask a doctor, pharmacist or health professionals if
 There is no improvement of symptoms after taking it for a few days
 you have following symptoms after use
■ Skin trouble: ■ rash, ■ itch, ■ bloodshot, and etc.
■ Digestive system disorder: ■ anorexia, ■stomach discomfort, ■nausea, ■vomiting, and etc.
■ Liver disorder: ■ jaundice, ■ fatigue, and etc.
■ Interstitial lung disease: ■ difficult to breathe, ■ fever, and etc. accompanied by ■ cough.
■ Urinary system disorder: ■ dysuria
■ The autonomic system disorder: ■ insomnia, ■ excessive sweating, ■ fast pulse, ■frequent urination, ■ palpitations, ■ feeling helplessness, ■ excitement, and etc.

Keep out of reach of the children.

INACTIVE INGREDIENT

Corn Starch, Animal originated ingredients: Lactose Hydrate/ Magnesium Stearate